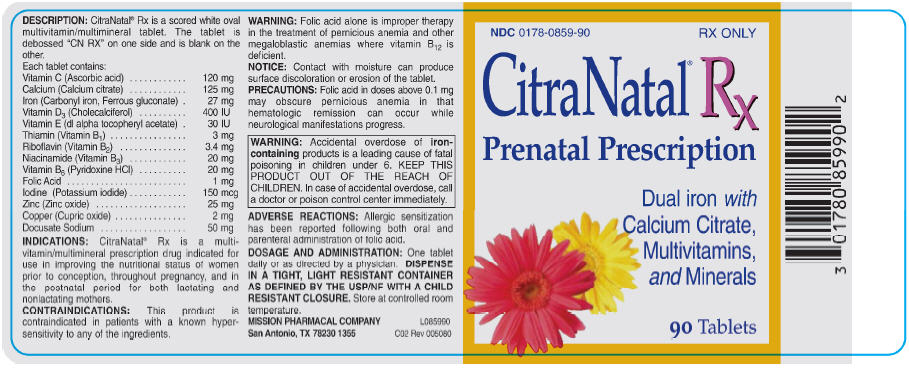 DRUG LABEL: CitraNatal Rx
NDC: 0178-0859 | Form: TABLET
Manufacturer: Mission Pharmacal Company
Category: prescription | Type: HUMAN PRESCRIPTION DRUG LABEL
Date: 20130321

ACTIVE INGREDIENTS: ASCORBIC ACID 120 mg/1 1; CALCIUM CITRATE 125 mg/1 1; IRON 27 mg/1 1; VITAMIN D 400 [iU]/1 1; .ALPHA.-TOCOPHEROL ACETATE 30 [iU]/1 1; THIAMINE 3 mg/1 1; RIBOFLAVIN 3.4 mg/1 1; NIACINAMIDE 20 mg/1 1; PYRIDOXINE HYDROCHLORIDE 20 mg/1 1; FOLIC ACID 1 mg/1 1; POTASSIUM IODIDE 150 mg/1 1; ZINC OXIDE 25 mg/1 1; CUPRIC OXIDE 2 mg/1 1; DOCUSATE SODIUM 50 mg/1 1
INACTIVE INGREDIENTS: POVIDONES 132.2 mg/1 1; FERROUS GLUCONATE 61.7 mg/1 1; ALPHA-TOCOPHERYLQUINONE 35.2 mg/1 1; MAGNESIUM SILICATE 10.38 mg/1 1; POLYETHYLENE GLYCOLS 1.98 mg/1 1; ETHYL VANILLIN .66 mg/1 1

CitraNatal® Rx

BOXED WARNING

Accidental overdose of iron-containing products is a leading cause of fatal poisoning in children under 6. KEEP THIS PRODUCT OUT OF THE REACH OF CHILDREN. In case of accidental overdose, call a doctor or poison control center immediately.

DESCRIPTION

CitraNatal® Rx is a scored white oval multivitamin/multimineral tablet. The tablet is debossed “CN RX” on one side and is blank on the other.

Each tablet contains:
Vitamin C (Ascorbic acid) | 120 mg
Calcium (Calcium citrate) | 125 mg
Iron (Carbonyl iron, ferrous gluconate) | 27 mg
Vitamin D3 (Cholecalciferol) | 400 IU
Vitamin E (dl-alpha tocopheryl acetate) | 30 IU
Thiamin (Vitamin B1) | 3 mg
Riboflavin (Vitamin B2) | 3.4 mg
Niacinamide (Vitamin B3) | 20 mg
Vitamin B6 (Pyridoxine) | 20 mg
Folic Acid | 1 mg
Iodine (Potassium iodide) | 150 mcg
Zinc (Zinc oxide) | 25 mg
Copper (Cupric oxide) | 2 mg
Docusate Sodium | 50 mg

INDICATIONS

CitraNatal® Rx is a multivitamin/multimineral prescription drug indicated for use in improving the nutritional status of women prior to conception, throughout pregnancy, and in the postnatal period for both lactating and nonlactating mothers.

CONTRAINDICATIONS

This product is contraindicated in patients with a known hypersensitivity to any of the ingredients.

WARNING

Folic acid alone is improper therapy in the treatment of pernicious anemia and other megaloblastic anemias where vitamin B12 is deficient.

NOTICE: Contact with moisture can produce surface discoloration or erosion of the tablet.

PRECAUTIONS

Folic acid in doses above 0.1 mg daily may obscure pernicious anemia in that hematologic remission can occur while neurological manifestations progress.

ADVERSE REACTIONS

Allergic sensitization has been reported following both oral and parenteral administration of folic acid.

DOSAGE AND ADMINISTRATION

One tablet daily or as directed by a physician. DISPENSE IN A TIGHT, LIGHT RESISTANT CONTAINER AS DEFINED BY THE USP/NF WITH A CHILD RESISTANT CLOSURE. Store at controlled room temperature.

L085990

C02 Rev 005080

MISSION PHARMACAL COMPANY
San Antonio, TX USA 78230 1355

CitraNatal® Rx Label
NDC: 0178-0859-90